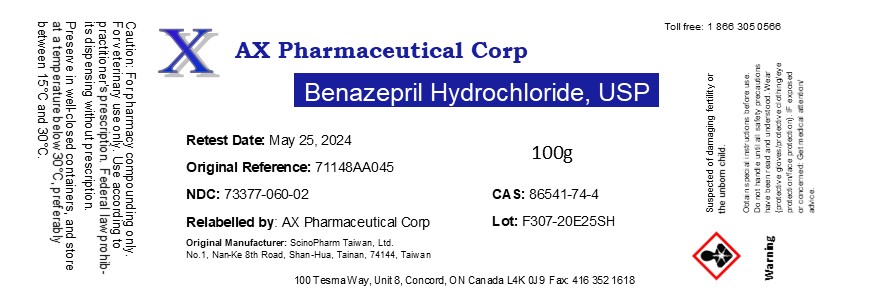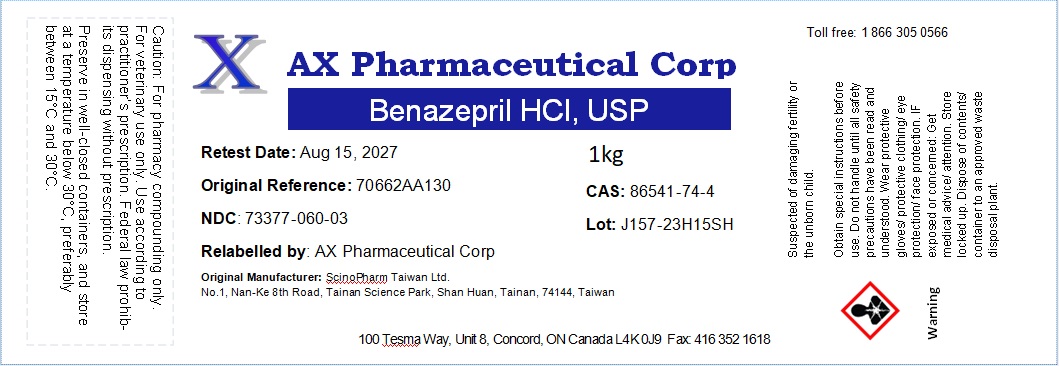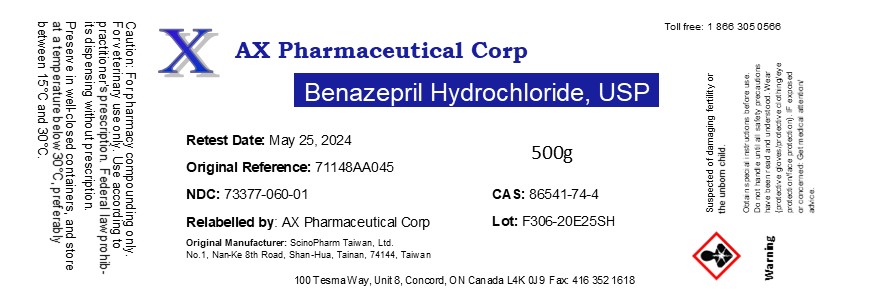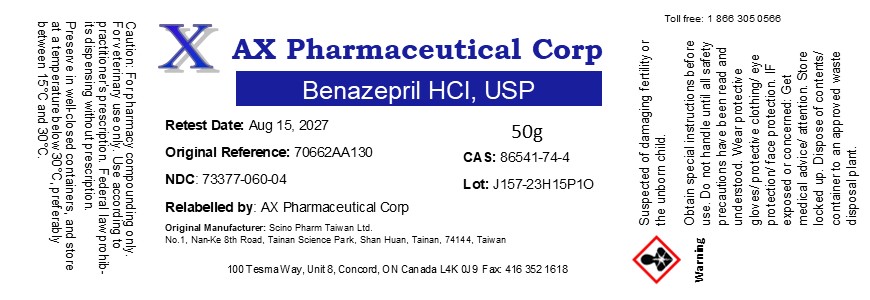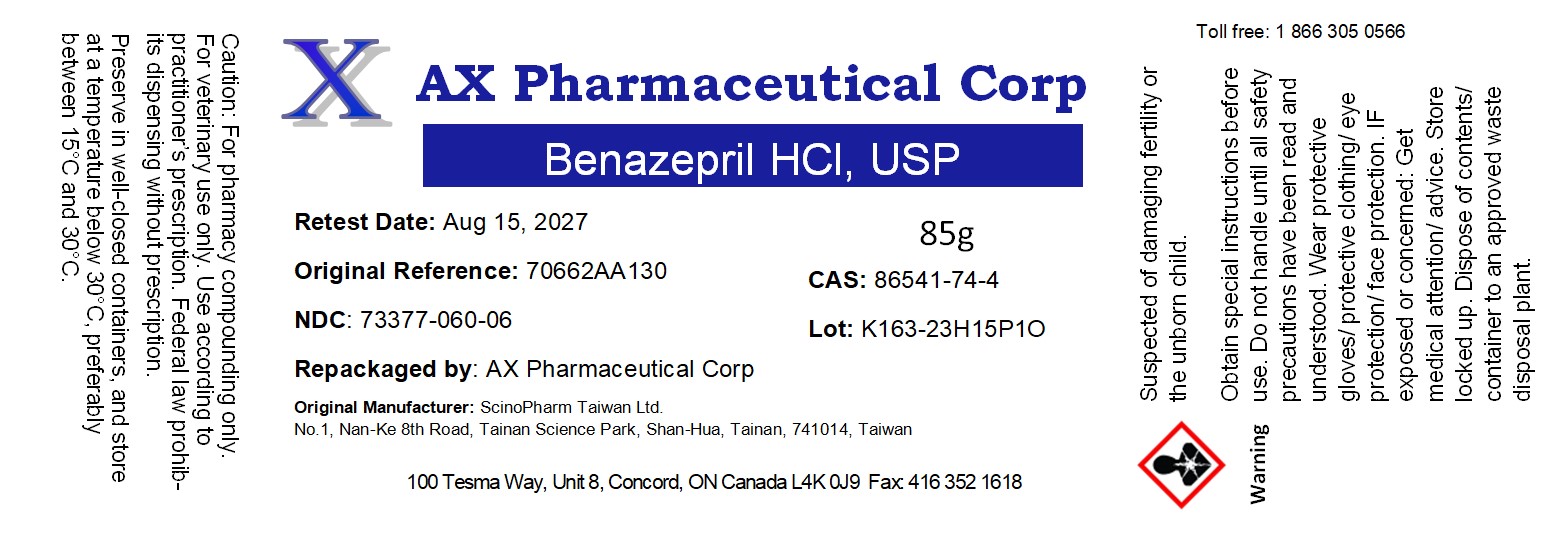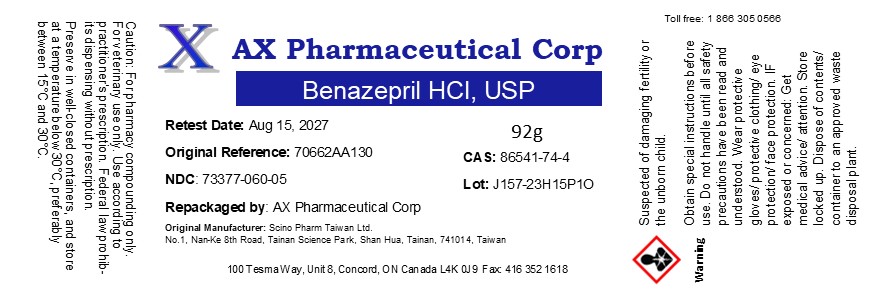 DRUG LABEL: Benazepril Hydrochloride
NDC: 73377-060 | Form: POWDER
Manufacturer: AX Pharmaceutical Corp
Category: other | Type: BULK INGREDIENT - ANIMAL DRUG
Date: 20250905

ACTIVE INGREDIENTS: BENAZEPRIL HYDROCHLORIDE 1 g/1 g

Benazepril Hydrochloride